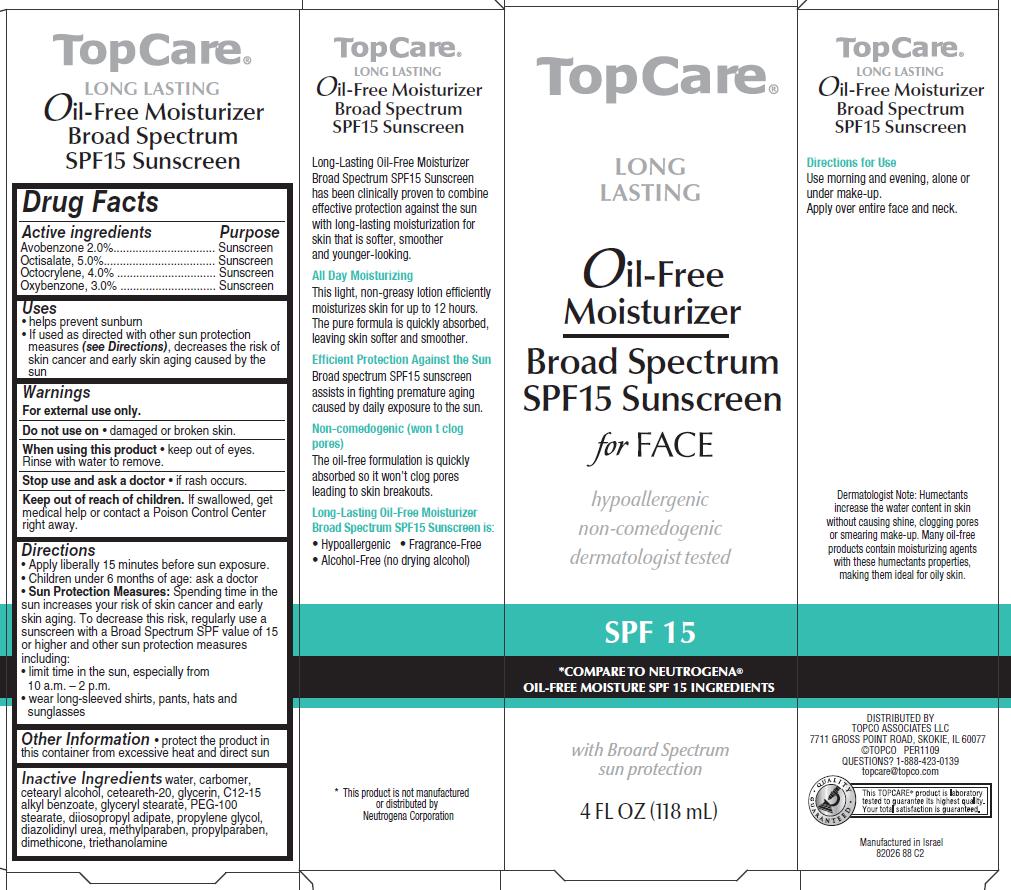 DRUG LABEL: Long-Lasting Oil-Free Moisturizer
NDC: 36800-360 | Form: CREAM
Manufacturer: Topco Associates LLC
Category: otc | Type: HUMAN OTC DRUG LABEL
Date: 20120511

ACTIVE INGREDIENTS: AVOBENZONE 2 mL/100 mL; OCTISALATE 5 mL/100 mL; OCTOCRYLENE 4 mL/100 mL; OXYBENZONE 3 mL/100 mL
INACTIVE INGREDIENTS: WATER; CARBOMER 1342; CETOSTEARYL ALCOHOL; POLYOXYL 20 CETOSTEARYL ETHER; GLYCERIN; ALKYL (C12-15) BENZOATE; GLYCERYL MONOSTEARATE; PEG-100 STEARATE; DIISOPROPYL ADIPATE; PROPYLENE GLYCOL; DIAZOLIDINYL UREA; METHYLPARABEN; PROPYLPARABEN; DIMETHICONE; TROLAMINE

TopCare® Long Lasting Oil-Free Moisturizer Broad Spectrum SPF15 Sunscreen for Face

Active ingredient

Avobenzone 2.0%
Octisalate 5.0%
Octocrylene 4.0%
Oxybenzone 3.0%

Purpose

Sunscreen

Uses

- helps prevent sunburn
- If used as directed with other sun protection measures (see Directions), decreases the risk of skin cancer and early skin aging caused by the sun

Warnings

For external use only.

Do not use on

- damaged or broken skin.

When using this product

- keep out of eyes. Rinse with water to remove.

Stop use and ask a doctor

- if rash occurs.

Keep Out of Reach of Children.

If swallowed, get medical help or contact a Poison Control Center right away.

Directions

- Apply liberally 15 minutes before sun exposure.
- Children under 6 months of age: ask a doctor
- Sun Protection Measures: Spending time in the sun increases your risk of skin cancer and early skin aging. To decrease this risk, regularly use a sunscreen with a Broad Spectrum SPF value of 15 or higher and other sun protection measures including:
  - limit time in the sun, especially from 10 a.m. - 2 p.m.
  - wear long-sleeved shirts, pants, hats and sunglasses

Other Information

- protect the product in this container from excessive heat and direct sun

Inactive ingredients

water, carbomer, cetearyl alcohol, ceteareth-20, glycerin, c12-15 alkyl benzoate, glyceryl stearate, peg-100 stearate, diisopropyl adipate, propylene glycol, diazolidinyl urea, methylparaben, propylparaben, dimethicone, triethanolamine

Questions?

1-888-423-0139

Package/Label Principal Display Panel

TopCare Long Lasting Oil-Free Moisturizer
Broad Spectrum SPF15 Sunscreen For FACE

Hypoallergenic
Non-comedogenic
Dermatologist tested

SPF 15
*compare to Neutrogena® Oil-Free Moisture SPF 15 Ingredients
With Broad Spectrum sun protection

4 FL OZ (118mL)

DISTRIBUTED BY TOPCO ASSOCIATES LLC
7711 GROSS POINT ROAD, SKOKIE, IL 60077
©TOPCO PER1109
QUESTIONS? 1-888-423-0139
topcare@topco.com

Manufactured in Israel
82026 88 C2

Carton Label